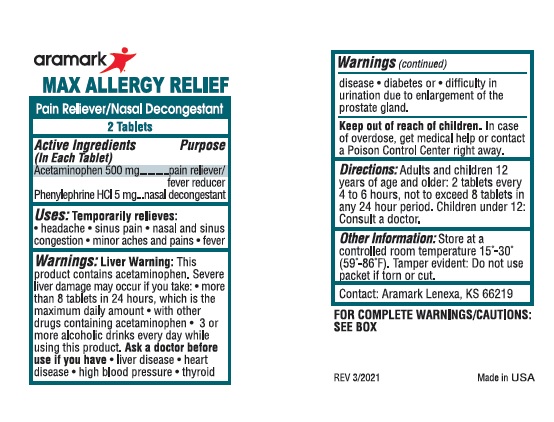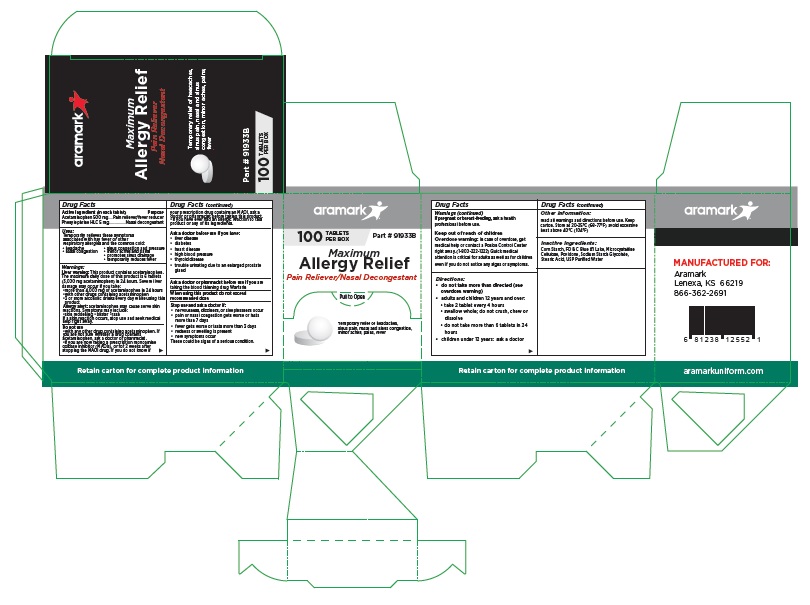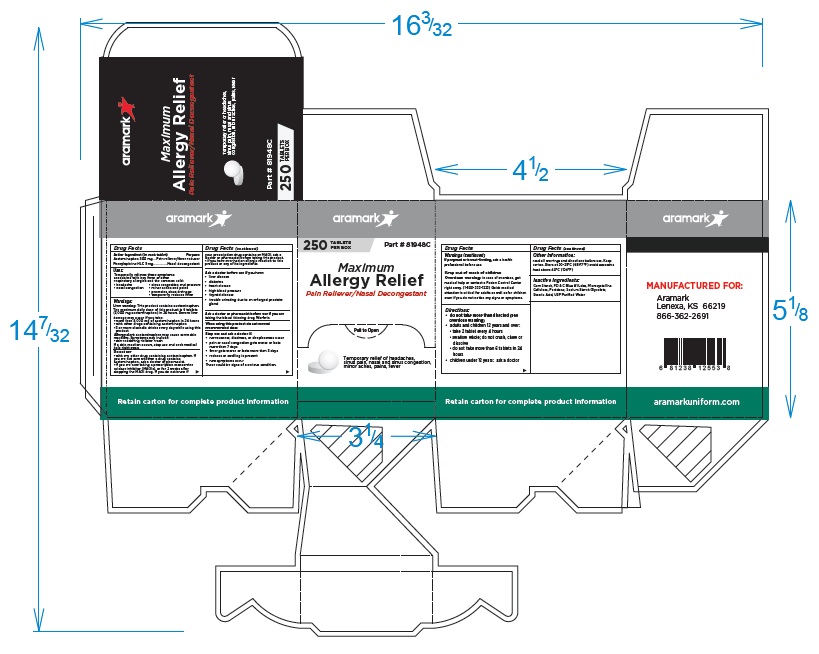 DRUG LABEL: Maximum Allergy Relief
NDC: 81238-0240 | Form: TABLET
Manufacturer: Western First Aid Safety DBA Aramark
Category: otc | Type: HUMAN OTC DRUG LABEL
Date: 20210611

ACTIVE INGREDIENTS: ACETAMINOPHEN 500 mg/1 1; PHENYLEPHRINE HYDROCHLORIDE 5 mg/1 1
INACTIVE INGREDIENTS: STARCH, CORN; FD&C BLUE NO. 1; MICROCRYSTALLINE CELLULOSE; POVIDONE; SODIUM STARCH GLYCOLATE TYPE A CORN; STEARIC ACID; WATER

Aramark Maximum Allergy Relief

Drug Facts

Active Ingredient (in each tablet)
Acetaminophen 500 mg
Phenylephrine HLC 5 mg

Purpose
Acetaminophen ...................Pain reliever/fever reducer
Phenylephrine HLC ................Nasal decongestant

Uses:
Temporarily relieves these symptoms
associated with hay fever or other
respiratory allergies and the common cold:

• headache • sinus congestion and pressure
• nasal congestion • minor aches and pains
• promotes sinus drainage
• temporarily reduces fever

Warnings:
Liver warning: This product contains acetaminophen.
The maximum daily dose of this product is 6 tablets
(3,000 mg acetaminophen) in 24 hours. Severe liver
damage may occur if you take:
•more than 4,000 mg of acetaminophen in 24 hours
•with other drugs containing acetaminophen
•3 or more alcoholic drinks every day while using this
product

Allergy alert: acetaminophen may cause serve skin
reactions. Symptoms may include:
•skin reddening •blister •rash
If a skin reaction occurs, stop use and seek medical
help right away

Do not use
•with any other drug containing acetaminophen. If
you are not sure whether a drug contains
acetaminophen, ask a doctor or pharmacist.
•if you are now taking a prescription monoamine
oxidase inhibitor (MAOIs), or for 2 weeks after
stopping the MAOI drug. If you do not know if
your prescription drug contains an MAOI, ask a
doctor or pharmacist before taking this product.
•if you have ever had an allergic reaction to this
product or any of its ingredients.

Ask a doctor before use if you have:
• liver disease
• diabetes
• heart disease
• high blood pressure
• thyroid disease
• trouble urinating due to an enlarged prostate
gland

Ask a doctor or pharmacist before use if you are
taking the blood thinning drug Warfarin

When using this product do not exceed
recommended dose

Stop use and ask a doctor if:
• nervousness, dizziness, or sleeplessness occur
• pain or nasal congestion gets worse or lasts
more than 7 days
• fever gets worse or lasts more than 3 days
• redness or swelling is present
• new symptoms occur
These could be signs of a serious condition.

If pregnant or breast-feeding, ask a health
professional before use.

Keep out of reach of children
Overdose warning: in case of overdose, get
medical help or contact a Poison Control Center
right away. (1-800-222-1222) Quick medical
attention is critical for adults as well as for children
even if you do not notice any signs or symptoms.

Directions:
• do not take more than directed (see
overdose warning)
• adults and children 12 years and over:
• take 2 tablet every 4 hours
• swallow whole; do not crush, chew or
dissolve
• do not take more than 6 tablets in 24
hours
• children under 12 years: ask a doctor

Other information:
read all warnings and directions before use. Keep
carton. Store at 20-25°C (68-77°F) avoid excessive
heat above 40°C (104°F)

Inactive Ingredients:
Corn Starch, FD & C Blue #1 Lake, Microcystalline
Cellulose, Povidone, Sodium Starch Glycolate,
Stearic Acid, USP Purified Water

Package Labeling

aramark

100 TABLETS Part # 91933B
PER BOX

Maximum
Allergy Relief
Pain Reliever/Nasal Decongestant

Temporary relief of headaches,
sinus pain, nasal and sinus congestion,
minor aches, pains, fever

MANUFACTURED FOR:

Aramark
Lenexa, KS 66219
(913) 269-9611

aramarkuniform.com

Retain carton for complete product information

100 Tablet Box

250 Tablet Box

2-Tablet Packet

res